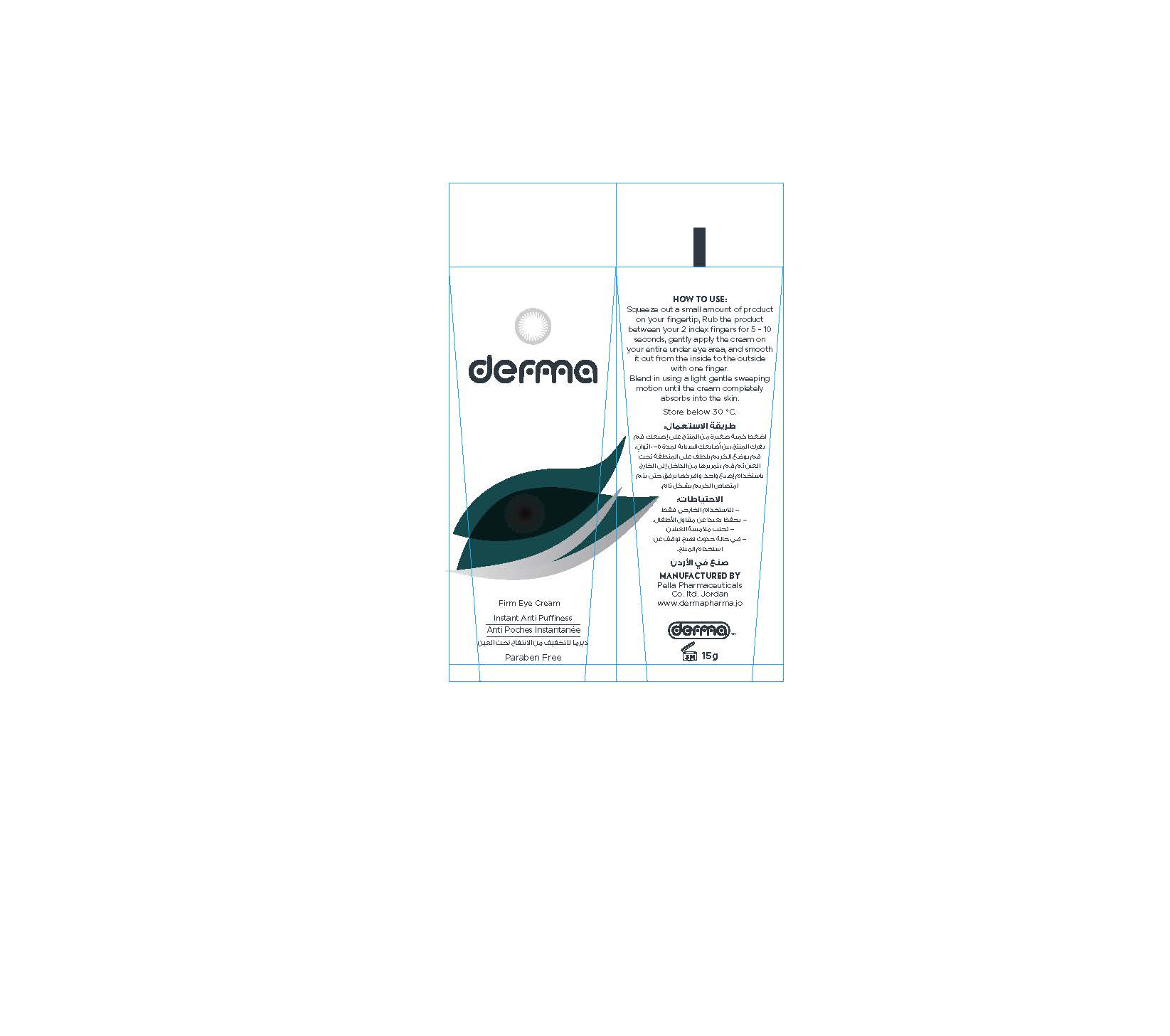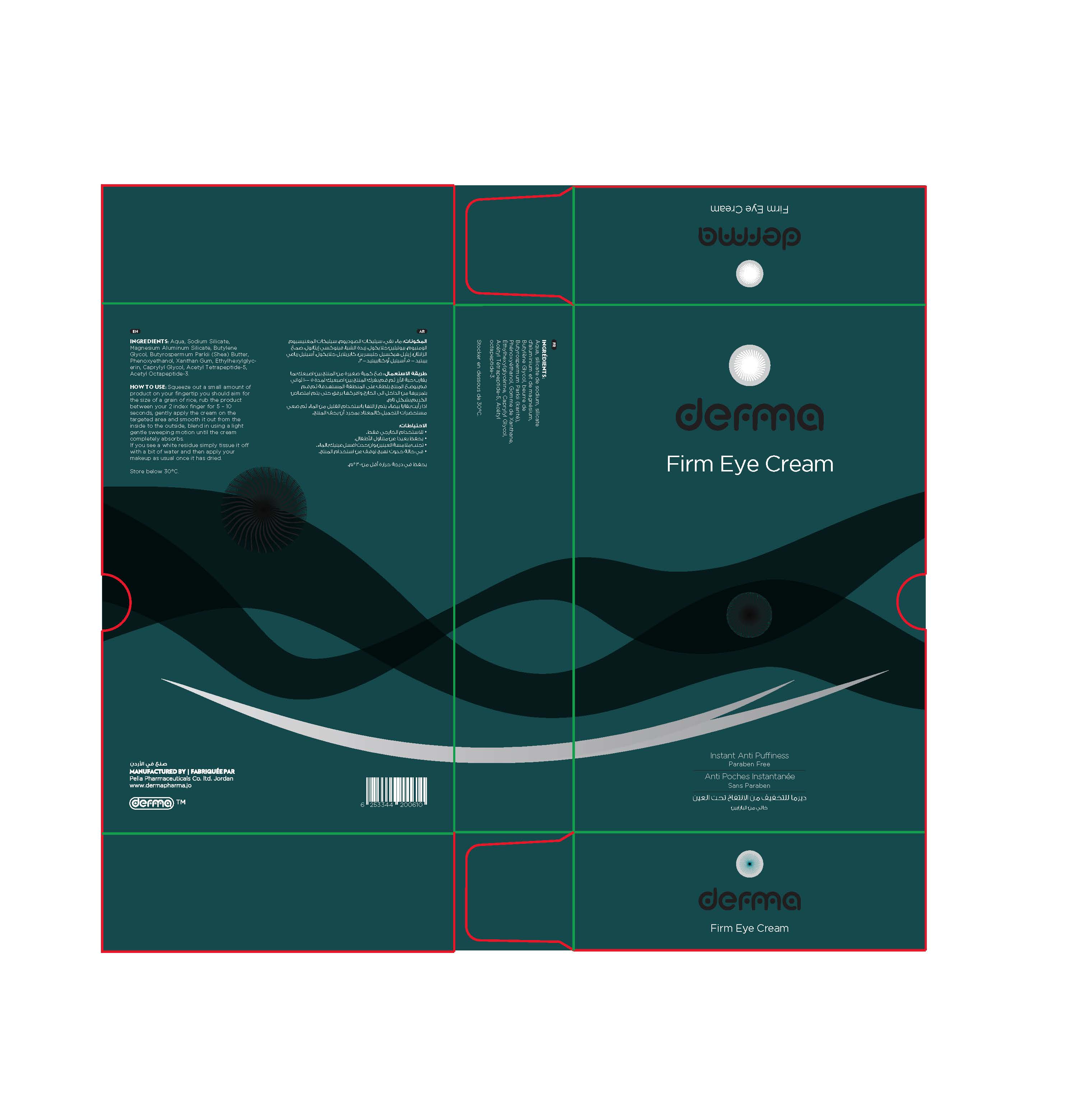 DRUG LABEL: Derma Firm Eye
NDC: 82160-610 | Form: CREAM
Manufacturer: Pella Pharmaceuticals Co. Ltd
Category: otc | Type: HUMAN OTC DRUG LABEL
Date: 20211118

ACTIVE INGREDIENTS: ACETYL TETRAPEPTIDE-5 0.0075 mg/15 g; ACETYL OCTAPEPTIDE-3 0.00375 mg/15 g
INACTIVE INGREDIENTS: XANTHAN GUM; WATER; CAPRYLYL GLYCOL; ETHYLHEXYLGLYCERIN; SODIUM SILICATE; MAGNESIUM ALUMINUM SILICATE; BUTYLENE GLYCOL; SHEA BUTTER; PHENOXYETHANOL

Firm Eye

Form and Presentation

Cream: Tube 15 g

Purpose

Instant Anti-Puffiness

Active Ingredients

Acetyl Tetrapeptide-5

Acetyl Octapeptide-3

Composition

Aqua, Sodium Silicate, Magnesium Aluminum Silicate, Butylene Glycol, Butyrospermum Parkii (Shea) Butter, Phenoxyethanol, Xanthan Gum, Ethylhexylglycerin, Caprylyl Glycol.

Properties

Derma firm eye is an effective Instant Anti-Puffiness which helps to diminish eye bags and the appearance of dark circles with just one single application per day.

Its revolutionary technology immediately targets eye bags and dark circles, by using a unique combination of clay minerals and a bi-peptide complex which will lead to strong skin tightening, a decrease of fluid accumulation under the eyes and a micro-muscular pause.

Perfume, dyes and paraben free.

Indication

Derma firm eye is specially formulated to address eye bags and dark circles around the delicate eye area

Contraindicatons

Hypersensitivity to any of the components

Precautions

- Must only be used as directed.
- Avoid excessive sun exposure.
- Do not use on damaged skin (e.g. open or infected wounds, third degree burns, acne, eczema). Only use on normal healthy, non-infected skin.
- To ensure optimal performance and to avoid dependence on the product, it is advised to allow the under-eye skin to rest a few days (4-5) after using the product daily for 4 weeks. In case of occasional use of the product there is no need for a resting period.
- Do not use if the packaging has been damaged.
- Not recommended for children under the age of 16.
- Once opened, it’s advised to use the product within 3 months.

Precaution

Keep out of reach of children

Warnings

- For external use only.
- Avoid contact with eyes. Rinse thoroughly with water in the event of contact with the eyes.
- Discontinue use if irritation (redness, pain, etc.) occurs. If skin irritation occurs, consult your physician if the symptoms persist for more than 48 hr.

Pregnancy

Not recommended for pregnant women

Lactation

Not recommended for breastfeeding women

Interactions

Oil-based makeup may reduce the effectiveness of the product

Side effects

Irritation (redness, pain, etc.) can occur

Dosage and administration

1. Wash your face gently and pat dry.
2. Apply an eye moisturizer (non-oil based) and wait for a minute or two so it can be completely absorbed into the skin.
3. Squeeze out a small amount of product on your fingertip. You should aim for the size of a grain of rice; any less will be not enough, and any more is generally too much and won’t be fully absorbed into the skin or could cause sensitivity.
4. Rub the product between your 2 index fingers for 5 – 10 seconds. Make sure there is still enough cream between the fingers. In case it doesn’t feel wet anymore, take a small amount on your fingertip again.
5. Gently apply the cream on your entire under eye area, and smooth it out from the inside to the outside with one finger. Blend in using a light gentle sweeping motion until the cream completely absorbs into the skin.
6. Remain expressionless for 2-3 minutes while the product dries to achieve dramatic results (fanning will accelerate the process). Simply tissue off the excess of cream with a bit of water if too much cream is applied. Wash hands and close the tube after use.

To Remove: Cleanse applied area with water and pat dry.

For under make up:

First, apply your usual products (eye serum, daily moisturizer, etc.) and allow time for these products to penetrate the layers of your skin (a minute or two). Then you can apply a very thin layer of derma firm eye to the targeted area as instructed.

Once the product has dried, apply your makeup as usual.

If you see a white residue you have either used too much product or did not use moisturizer. Simply tissue off the white residue with a bit of water.

- Only use once a day. Do not use the product continuously for more than 4 weeks.
- The effects will last anywhere from 8 – 10 hours on average, without makeup the effects can last longer.

Storage Condition

Store below 30◦C